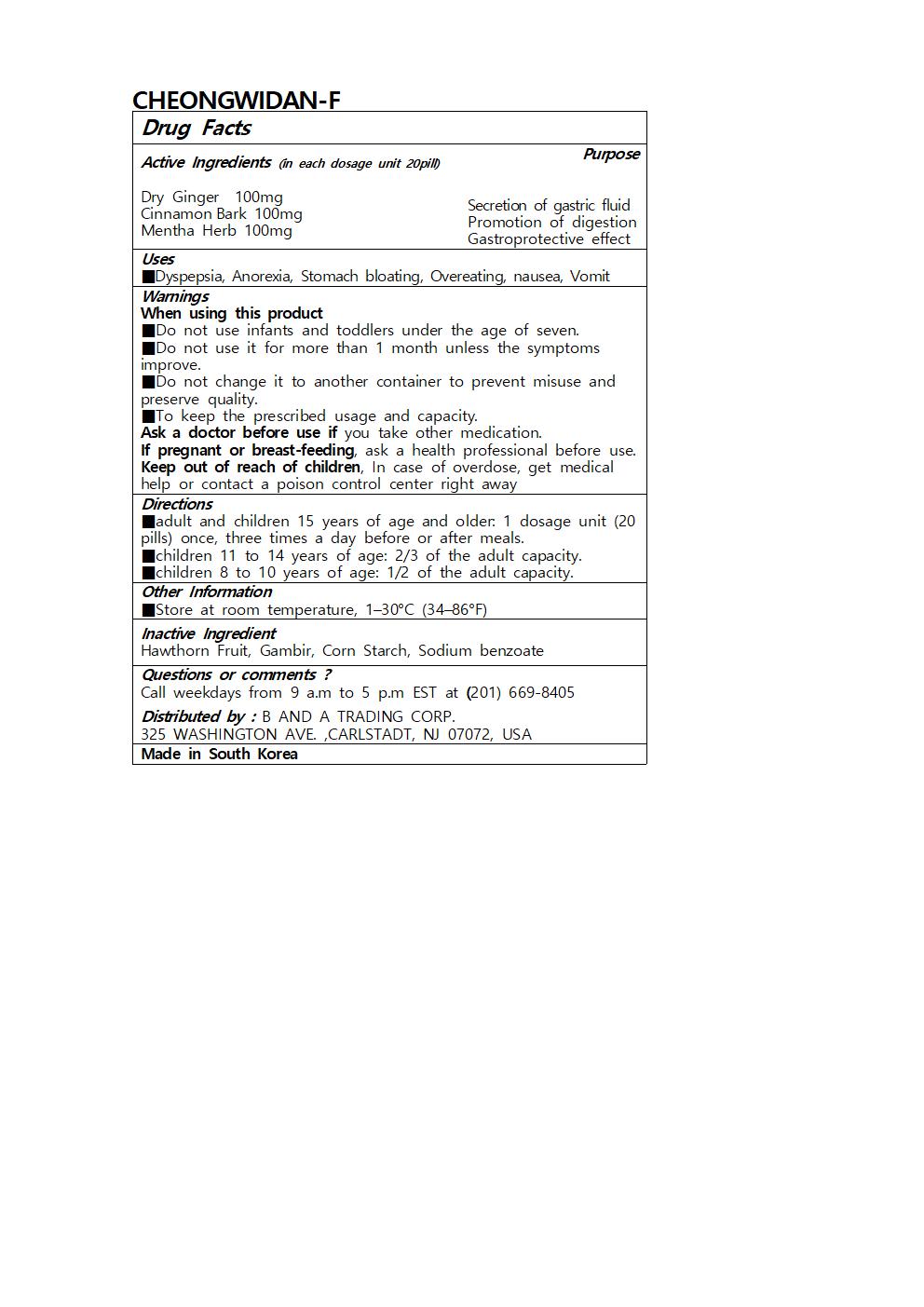 DRUG LABEL: CHEONGWIDAN-F
NDC: 73466-0034 | Form: PILL
Manufacturer: MISOCOS
Category: otc | Type: HUMAN OTC DRUG LABEL
Date: 20250301

ACTIVE INGREDIENTS: GINGER 100 mg/20 1; CINNAMON 100 mg/20 1
INACTIVE INGREDIENTS: SODIUM BENZOATE; MENTHA ARVENSIS TOP

Drug Facts

ACTIVE INGREDIENT

Dry Ginger 100mg

CinnamonBark 100mg

Mentha Herb 100mg

INACTIVE INGREDIENT

Hawthorn Fruit, Gambir, Corn Starch, Sodium benzoate

PURPOSE

■Dyspepsia, Anorexia, Stomach bloating, Overeating, nausea, Vomit

keep out of reach of the children

Directions

■adult and children 15 years of age and older: 1 dosage unit (20 pills) once, three times a day before or after meals.

■children 11 to 14 years of age: 2/3 of the adult capacity.

■children 8 to 10 years of age: 1/2 of the adult capacity.

When using this product

■Do not use infants and toddlers under the age of seven.

■Do not use it for more than 1 month unless the symptoms improve.

■Do not change it to another container to prevent misuse and preserve quality.

■To keep the prescribed usage and capacity.

Ask a doctor before use if you take other medication.

If pregnant or breast-feeding, ask a health professional before use.

Keep out of reach of children, In case of overdose, get medical help or contact a poison control center right away

DOSAGE AND ADMINISTRATION

for oral use only